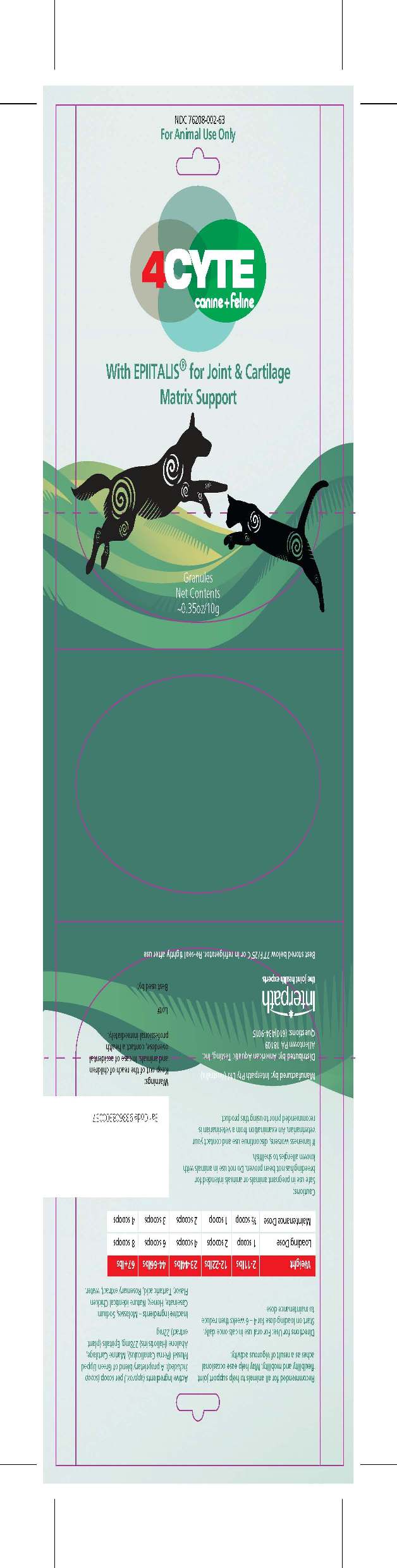 DRUG LABEL: Canine and Feline with Epiitalis for Joint and Cartilage Matrix Support
NDC: 76208-002 | Form: GRANULE
Manufacturer: American Aquatic Testing, Inc.
Category: animal | Type: OTC ANIMAL DRUG LABEL
Date: 20110826

ACTIVE INGREDIENTS: NEW ZEALAND GREEN MUSSEL 408 mg/1 g; BLACKFOOT ABALONE 136 mg/1 g; SHARK 136 mg/1 g; PLATYCLADUS ORIENTALIS SEED 54 mg/1 g

4CYTE Canine and Feline with Epiitalis for Joint and Cartilage Matrix Support

NDC 76208-002-63
For Animal Use Only
4CYTE
CANINE ANDFELINE with
EPIITALIS for Joint and
Cartilage Matrix Support
Granules
Net Contents
~0.35oz (10g) sachet
Lot No.
Best used by:
Manufactured by: Interpath Pty. Ltd. (Australia)
Distributed by: American Aquatic Testing, Inc.
Allentown, PA 18109
Questions: (610)434-9015

INDICATIONS AND USAGE

Recommended for all animals to help support joint flexibility and mobility.
May help ease occasional aches as a result of vigorous activity,
such as agility or performance racing.

Active Ingredients (approx.) per scoop (scoop included)
A proprietary blend of Green Lipped Mussel (Perna
Canaliculus),Abalone (Haliotis iris),
Marine Cartilage…………………………………….278mg
Epiitalis (plant extract) ……………………………22mg

DOSAGE AND ADMINISTRATION

Directions for Use: For oral use in dogs and cats once daily.
Start on loading dose for 4 – 6 weeks then reduce to maintenance dose

Weight 2 – 11lbs 12 -22lbs 23 – 44lbs 45 – 66lbs 67+ lbs
Loading Dose 1 scoop 2 scoops 4 scoops 6 scoops 8 scoops
Maintenance Dose ½ Scoop 1 scoop 2 scoops 3 scoops 4 scoops

WARNINGS AND PRECAUTIONS

Cautions:
Safe use in pregnant animals or animals intended for breeding has not been proven.
Do not use in animals with known allergies to shellfish.
If lameness worsens, discontinue use and contact your veterinarian.
An examination from a veterinarian is recommended prior to using this product.
Warnings:
Keep out of the reach of children and animals. In case of
accidental overdose, contact a
health professional immediately

STORAGE AND HANDLING

Best stored below 77˚F/25˚C or in refrigerator. Re-seal tightly after use

Canine and Feline Label